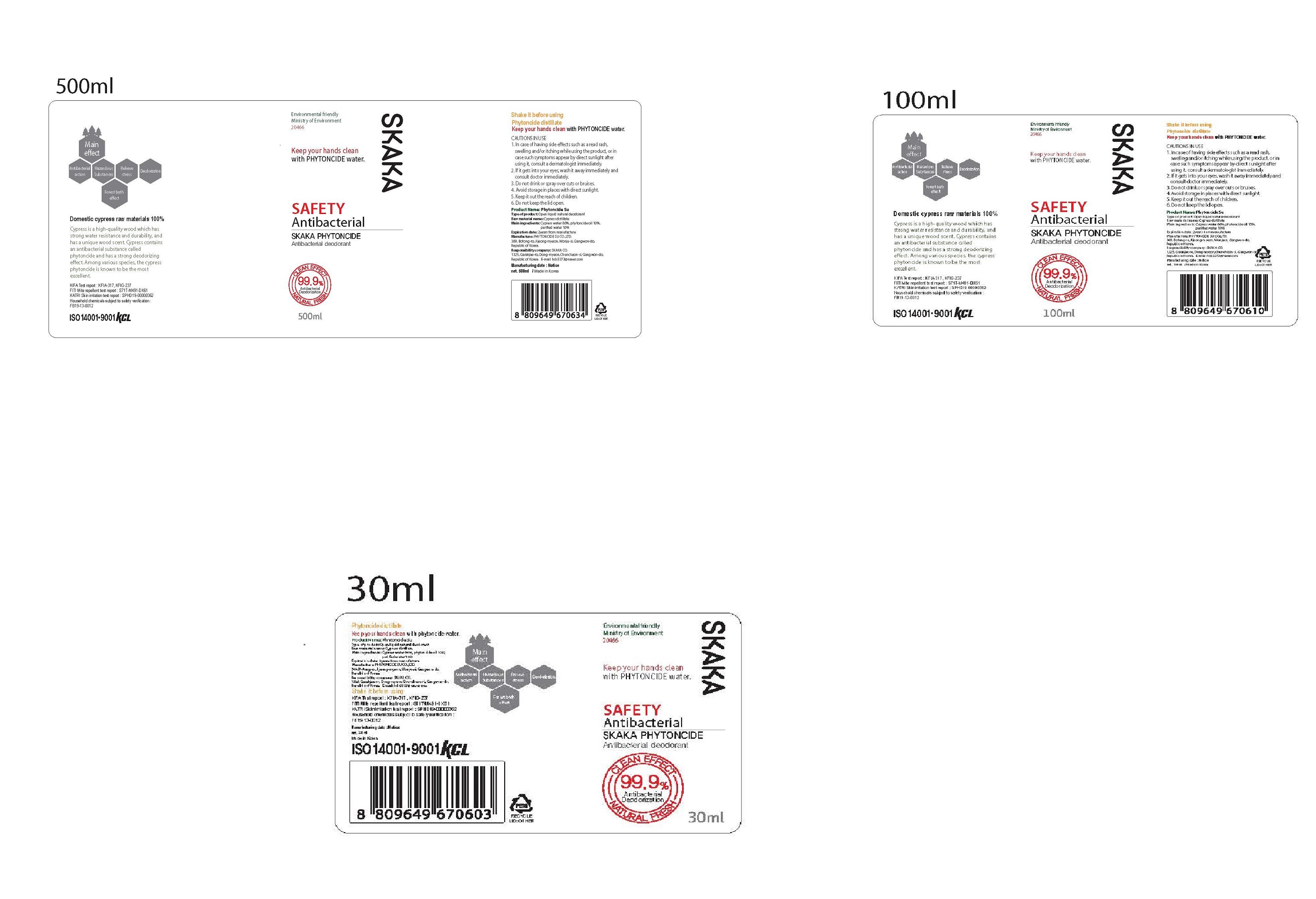 DRUG LABEL: SKAKA PHYTONCIDE
NDC: 75194-002 | Form: LIQUID
Manufacturer: Phytoncide Su Co LTD
Category: otc | Type: HUMAN OTC DRUG LABEL
Date: 20200523

ACTIVE INGREDIENTS: CHAMAECYPARIS OBTUSA WOOD OIL 10 g/100 mL
INACTIVE INGREDIENTS: WATER; CHAMAECYPARIS OBTUSA WHOLE

Drug Facts

ACTIVE INGREDIENT

Cypress distillate

INACTIVE INGREDIENT

Cypress water
phytoncide oil
purified water

PURPOSE

Cypress is a high-quality wood that has
strong water resistance and durability,
and has a unique wood scent. Cypress
contains an antibacterial substance called
phytoncide and has a strong deodorizing
effect. Among various species, the cypress
phytoncide is known to be the most
excellent.

KEEP OUT OF REACH OF THE CHILDREN

INDICATIONS AND USAGE

Put Phytoncide extract cypress water in a spray container and spray it all over the house.It captures unpleasant odors in the house, removes house dust mites, and has excellent antibacterial and deodorizing effects.It is made of natural materials, no harm to human body, relieve itching of the skin, improve rhinitis and asthma,If you smell the scent, you can reduce the stress hormone and you can feel the healing effect of forest bath in a recreational forest.To get a sleep effect, spray it before you sleep. Eliminates various oders from food, blankets and wardrobes..

WARNINGS

Precautions
1. It is harmless to human body, but do not drink it
2. Avoid direct sunlight and store in a cool place
3. Keep it in a closed place in children's hands
4. Do not keep the lid open.
First Aid General
If medical action is required, show the product's container
or labeling information, and if you feel uncomfortable with
exposure to the product, a medical institution (please seek
help from a doctor)
Oral exposure: If it gets into your eyes, wash it away
immediately and consult your doctor if you have any
abnormalities.
Quality management and quality labeling under the
Industrial Products Safety Management Act

DOSAGE AND ADMINISTRATION

for external use only